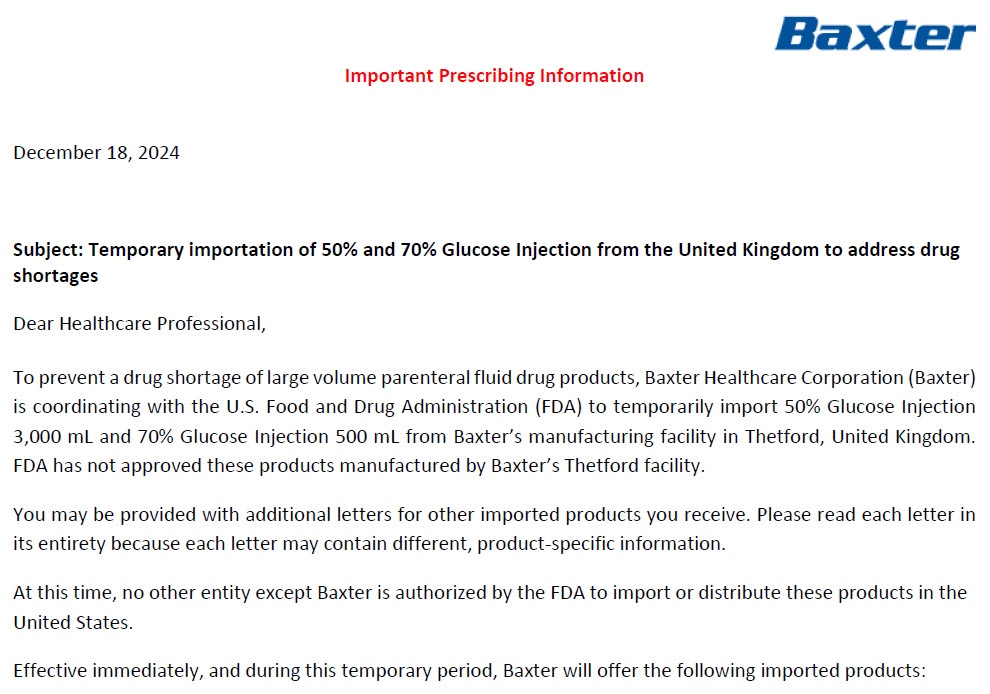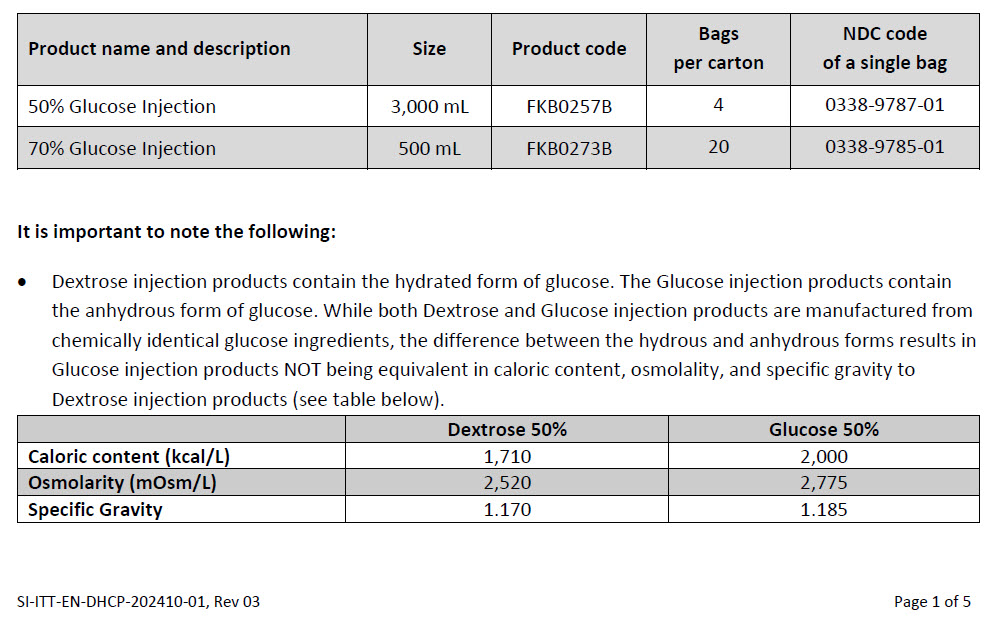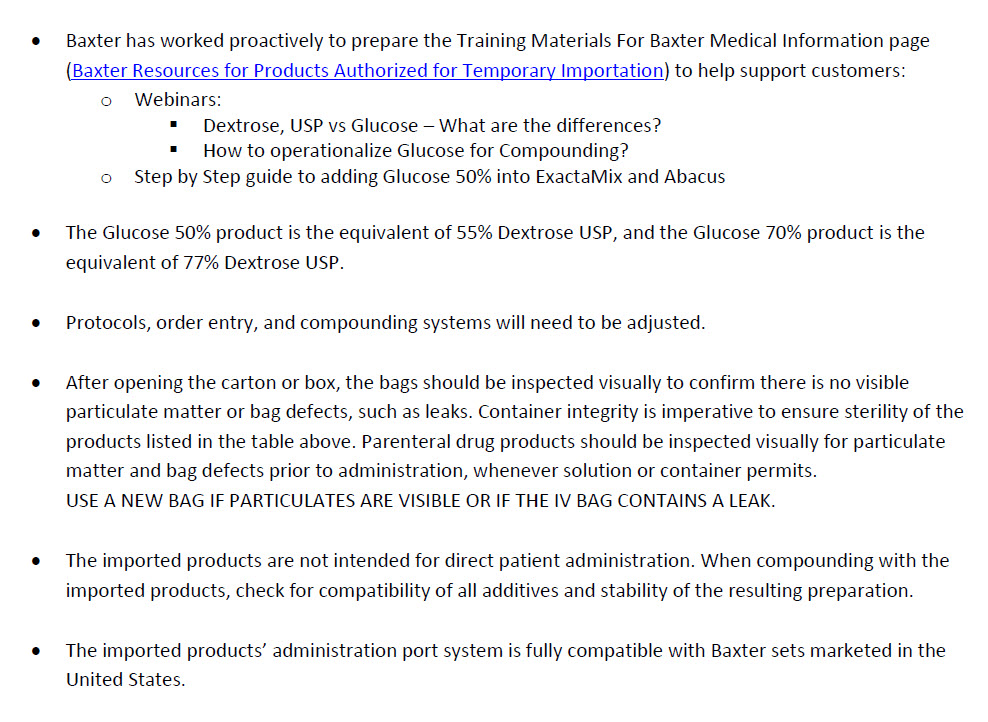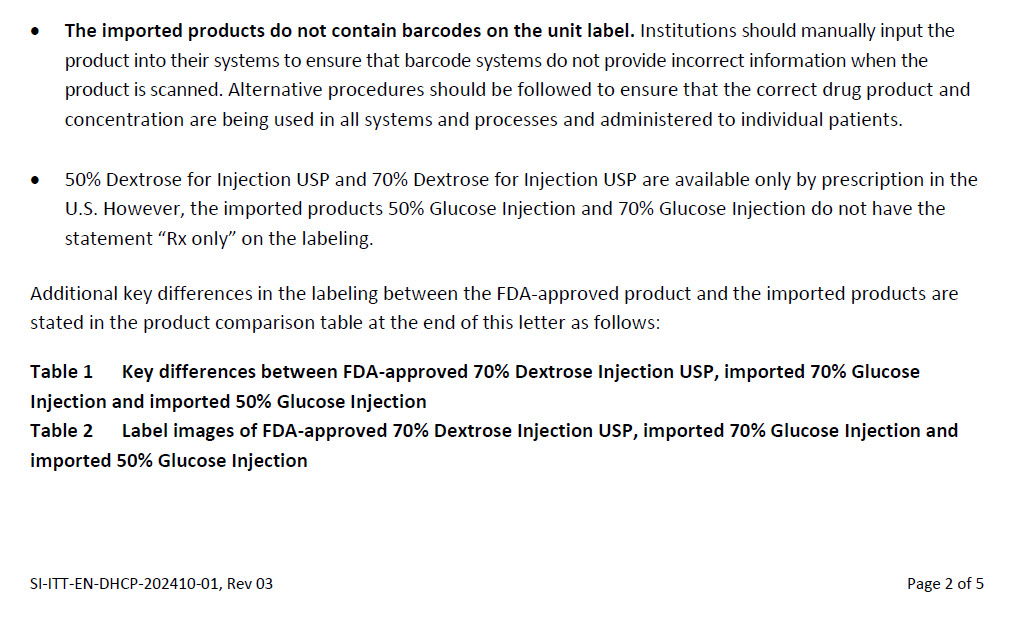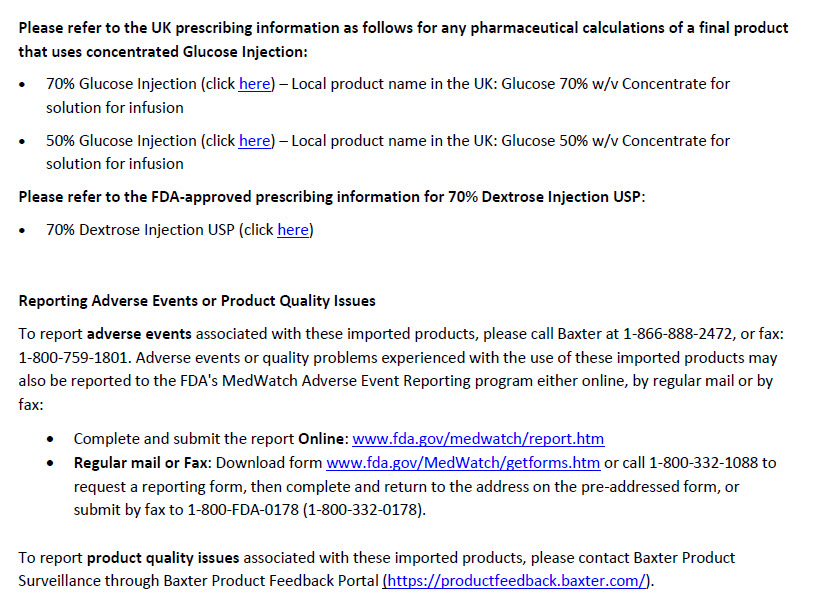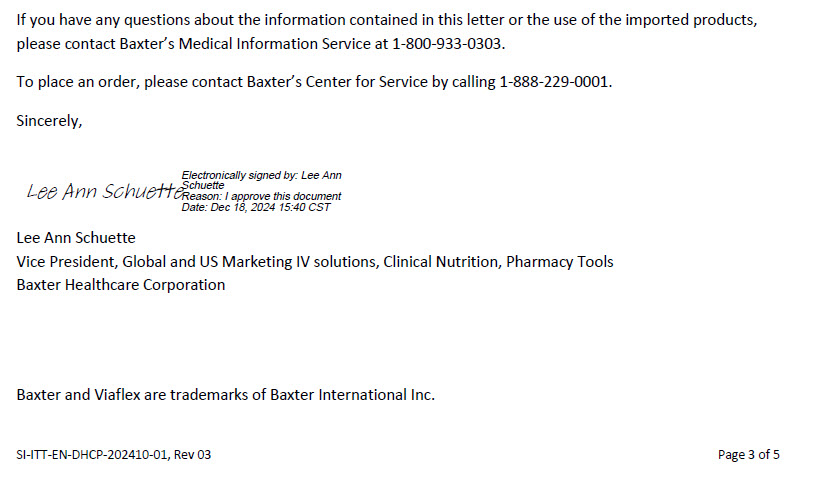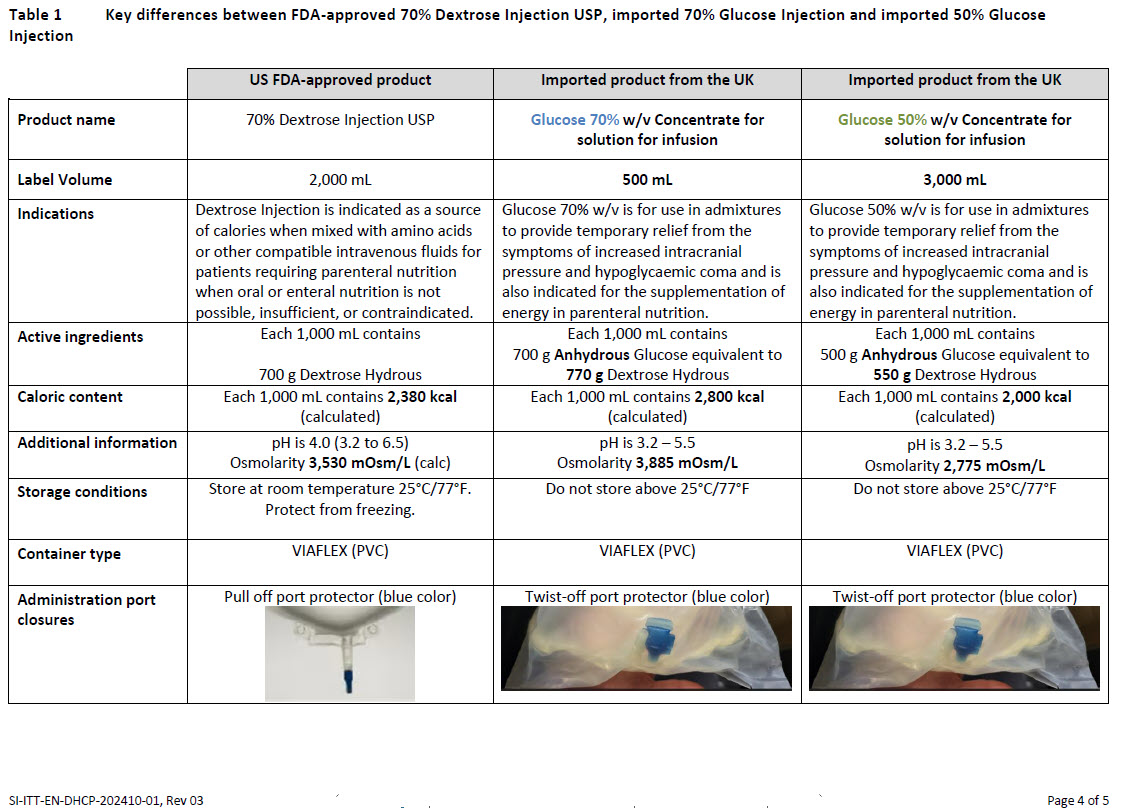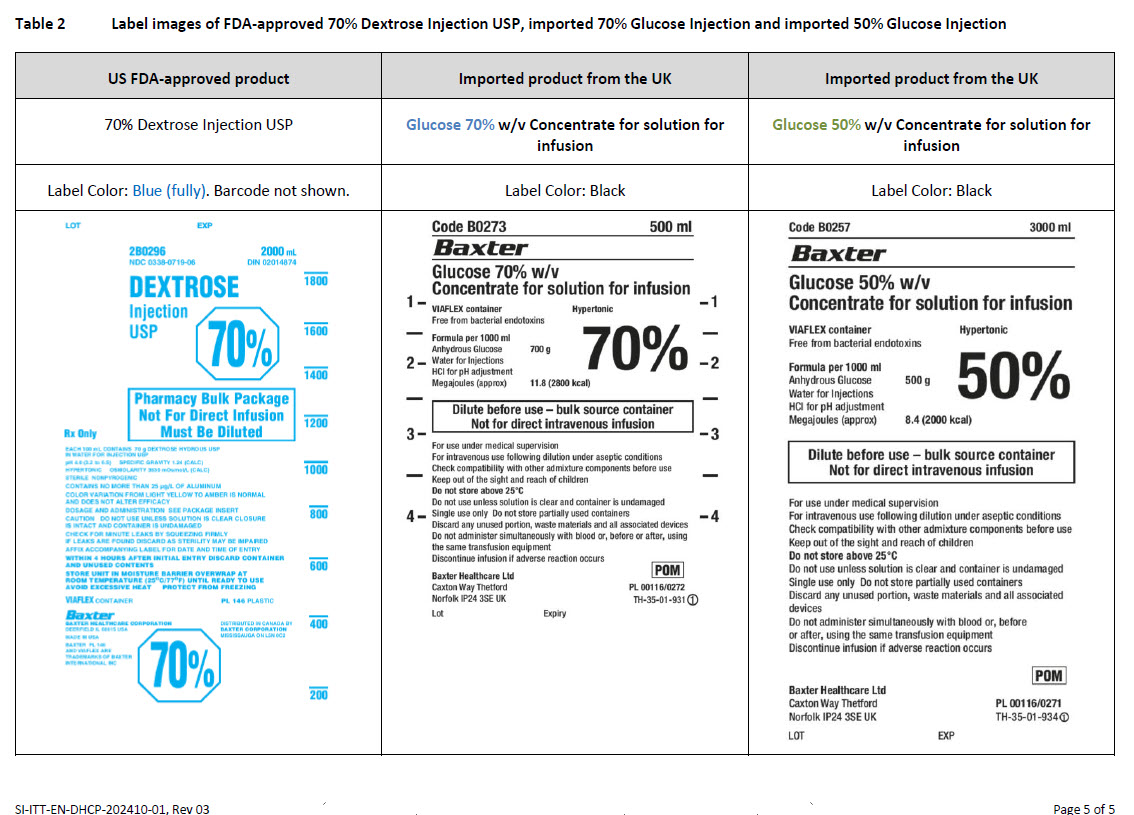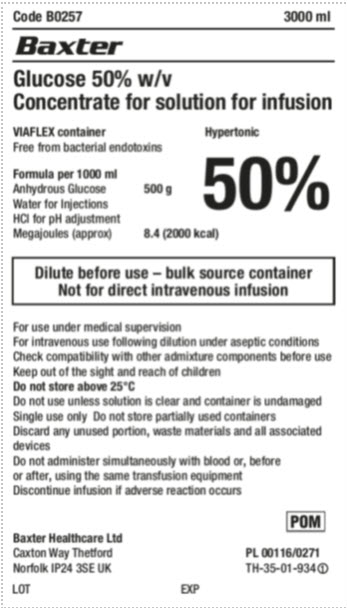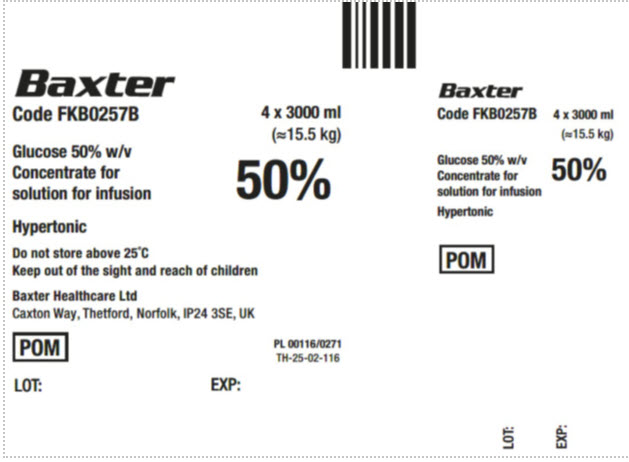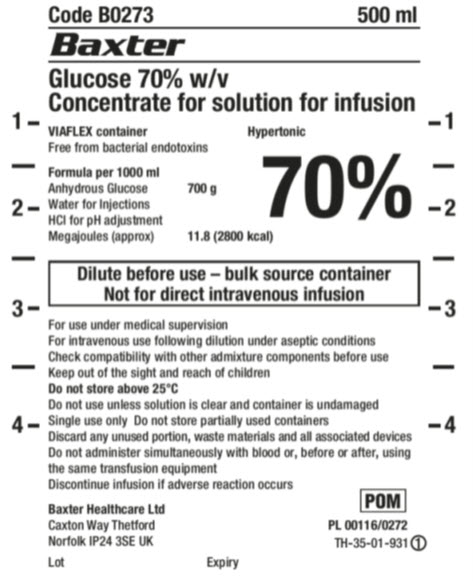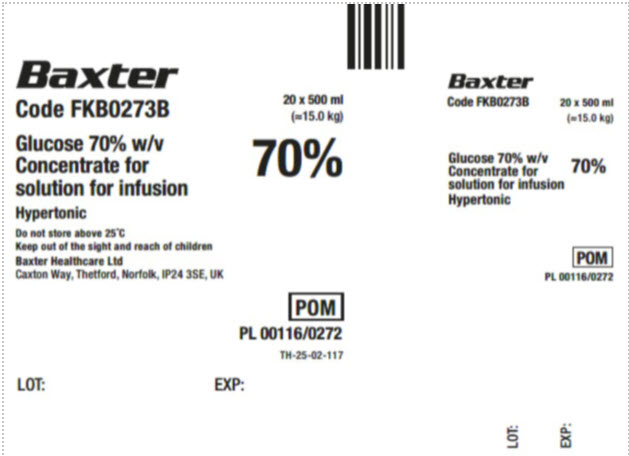 DRUG LABEL: Glucose
NDC: 0338-9787 | Form: INJECTION, SOLUTION
Manufacturer: Baxter Healthcare Company
Category: prescription | Type: HUMAN PRESCRIPTION DRUG LABEL
Date: 20241218

ACTIVE INGREDIENTS: DEXTROSE MONOHYDRATE 55 g/100 mL
INACTIVE INGREDIENTS: WATER; HYDROCHLORIC ACID

50% and 70% glucose injection

Health Care Professional Letter

Baxter has worked proactively to prepare the Training Materials for Baxter Medical Information page (https://meded.baxter.com/hurricane-helene-clinical-resources/baxter-resources-for-products-authorized-for-temporary-importation)

Please refer to the UK prescribing information as follows for any pharmaceutical calculations of a final product that uses concentrated Glucose injection:

- 70% Glucose Injection (click https://mhraproducts4853.blob.core.windows.net/docs/6be6cb79cc56be57f99cfd218cfbd1b34bca8047)) – Local product name in the UK: Glucose 70% w/v Concentrate for solution for infusion
- 50% Glucose Injection (click https://mhraproducts4853.blob.core.windows.net/docs/6d79a27acece3f48020b83e2b3716a2353b6f8b3) – Local product name in the UK: Glucose 50% w/v Concentrate for solution for infusion

Please refer to the FDA-approved prescribing information for the 70% Dextrose Injection USP:

- 70% Dextrose Injection USP (click https://dailymed.nlm.nih.gov/dailymed/drugInfo.cfm?setid=0332f34a-7038-47cc-ba59-d55cad6b73ca)

Reporting Adverse Events or Product (Quality Issues)

To report adverse events associated with these imported products, please call Baxter at 1-866-888-2472, or fax: 1-800-759-1801. Adverse events or quality problems experienced with the use of these imported products may also be reported to the FDA's MedWatch Adverse Event Reporting program either online, by regular mail or by fax:

- Complete and submit the report Online: www.fda.gov/medwatch/report.htm
- Regular mail or Fax: Download form www.fda.gov/MedWatch/getforms.htm or call 1-800-332-1088 to request a reporting form, then complete and return to the address on the pre-addressed form, or submit by fax to 1-800-FDA-0178 (1-800-332-0178).

To report product quality issues associated with these imported products, please contact Baxter Product Surveillance through Baxter Product Feedback Portal (https://productfeedback.baxter.com/).

PACKAGE/LABEL PRINCIPAL DISPLAY PANEL

Container Label

Code B0257 3000 ml

Baxter Logo

Glucose 50% w/v
Concentrate for solution for infusion

VIAFLEX container Hypertonic
Free from bacterial endotoxins

Formula per 1000 ml
Anhydrous Glucose
Water for Injections
HCI for pH adjustment
Megajoules (approx.)

500 g

8.4 (2000 kcal)

50%

Dilute before use – bulk source container
Not for direct intravenous infusion

For use under medical supervision
For intravenous use following dilution under aseptic conditions
Check compatibility with other admixture components before use
Keep out of the sight and reach of children
Do not store above 25°C
Do not use unless solution is clear and container is undamaged
Single use only Do not store partially used containers
Discard any unused portion, waste materials and all associated
devices
Do not administer simultaneously with blood or, before
or after, using the same transfusion equipment
Discontinue infusion if adverse reaction occurs

Baxter Healthcare Ltd
Caxton Way Thetford
Norfolk IP24 3SE UK

LOT EXP

POM

PL 00116/0271
TH-35-01-934

Carton Label

Baxter Logo
Code FKB0257B

Glucose 50% w/v
Concentrate for
solution for infusion

Hypertonic

Do not store above 25°C
Keep out of sight and reach of children

Baxter Healthcare Ltd
Caxton Way, Thetford, Norfolk, IP24 3SE, UK

POM

LOT: EXP:

4 x 3000 ml
(≈15.5 kg)

50%

PL 00116/0271
TH-25-02-116

Baxter Logo
Code FKB0257B

Glucose 50% w/v
Concentrate for
solution for infusion

Hypertonic

POM

4 x 3000 ml
(≈15.5 kg)

50%

LOT: EXP:

Container Label

1 –

-

2-

-

3-

-

4-

Code B0273 500 ml

Baxter Logo

Glucose 70% w/v
Concentrate for solution for infusion

VIAFLEX container Hypertonic
Free from bacterial endotoxins

Formula per 1000 ml
Anhydrous Glucose
Water for Injections
HCI for pH adjustment
Megajoules (approx.)

700 g

11.8 (2800 kcal)

70%

Dilute before use – bulk source container
Not for direct intravenous infusion

For use under medical supervision
For intravenous use following dilution under aseptic conditions
Check compatibility with other admixture components before use
Keep out of the sight and reach of children
Do not store above 25°C
Do not use unless solution is clear and container is undamaged
Single use only Do not store partially used containers
Discard any unused portion, waste materials and all associated devices
Do not administer simultaneously with blood or, before or after, using
the same transfusion equipment
Discontinue infusion if adverse reaction occurs

Baxter Healthcare Ltd
Caxton Way Thetford
Norfolk IP24 3SE UK

Lot Expiry

POM
PL 00116/0272
TH-35-01-931

-1

-

-2

-

-3

-

-4

Carton Label

Baxter Logo
Code FKB0273B

Glucose 70% w/v
Concentrate for
solution for infusion

Hypertonic

Do not store above 25°C
Keep out of sight and reach of children

Baxter Healthcare Ltd
Caxton Way, Thetford, Norfolk, IP24 3SE, UK

LOT: EXP:

20 x 500 ml
(≈15.0 kg)

70%

POM
PL 00116/0272
TH-25-02-117

Baxter Logo
Code FKB0273B

Glucose 70% w/v
Concentrate for
solution for infusion

Hypertonic

20 x 500 ml
(≈15.0 kg)

70%

POM
PL 00116/0272

LOT: EXP: